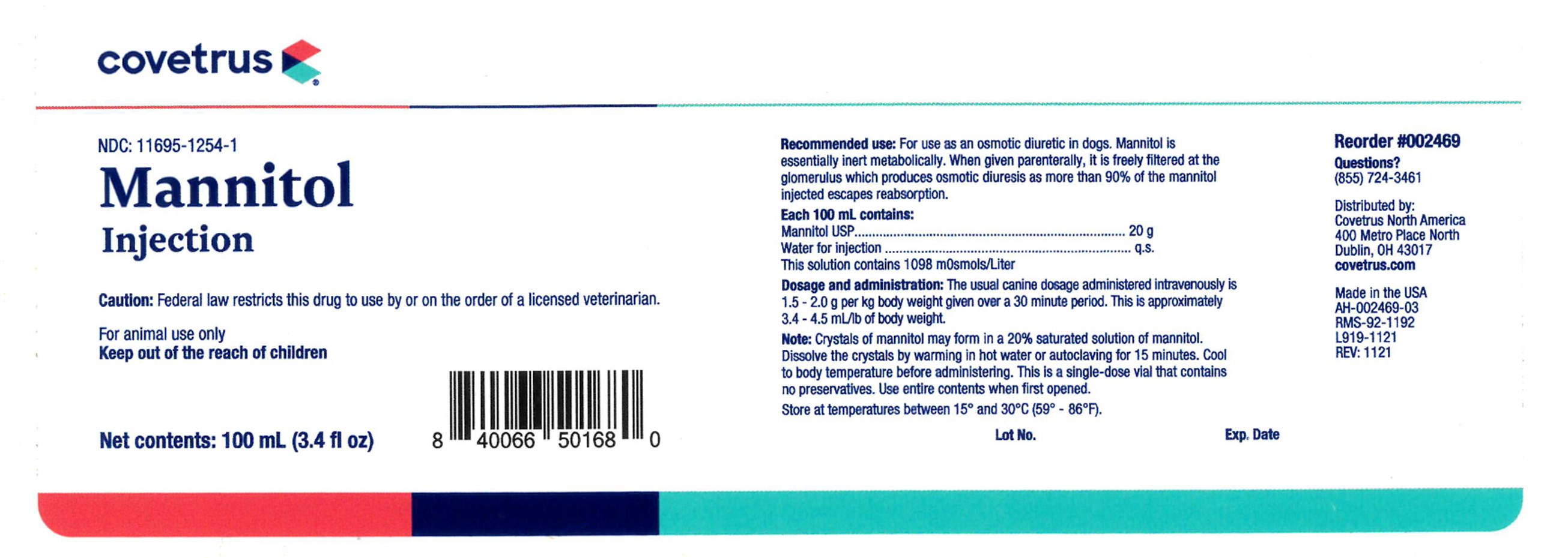 DRUG LABEL: Mannitol
NDC: 11695-1254 | Form: INJECTION
Manufacturer: Covetrus
Category: animal | Type: PRESCRIPTION ANIMAL DRUG LABEL
Date: 20221223

ACTIVE INGREDIENTS: MANNITOL 20 g/100 mL
INACTIVE INGREDIENTS: WATER

Covetrus
Mannitol

Recommended Use:

For use as an osmotic diuretic in dogs. Mannitol is essentially inert metabolically. When given parenterally, it is freely filtered at the glomerulus which produces osmotic diuresis as more than 90% of the mannitol injected escapes reabsorption.

Each 100 mL Contains:

Mannitol USP...................................20 g

Water for Injection...........................q.s.

This solution contains 1098 mOsmols/Liter

Dosage and administration:

The usual canine dosage administered intravenously is 1.5 - 2.0 g per kg body weight given over a 30 minute period. This is approximately 3.4-4.5 mL/lb of body weight.

Note:

Crystals of mannitol may form in a 20% saturated solution of mannitol. Dissolve the crystals by warming in hot water or autoclaving for 15 minutes. Cool to body temperature before administering. This is a single dose vial that contains no preservatives. Use entire contents when first opened.

STORAGE AND HANDLING

Store at temperatures between 15°and 30°C (59°-86°F).

NDC:11695-1254-1

Net contents: 100 mL (3.4 fl oz)

Lot No.

Exp. Date

Reorder #002469

Questions?

(855) 724-3461

Distributed by:

Covetrus North America

400 Metro Place North

Dublin, OH 43017

covetrus.com

Made in the USA

AH-002469-03

RMS-92-1192

L919-1121

REV: 1121

Caution:

Federal law restricts this drug to use by or on the order of a licensed veterinarian.

FOR ANIMAL USE ONLY

KEEP OUT OF THE REACH OF CHILDREN